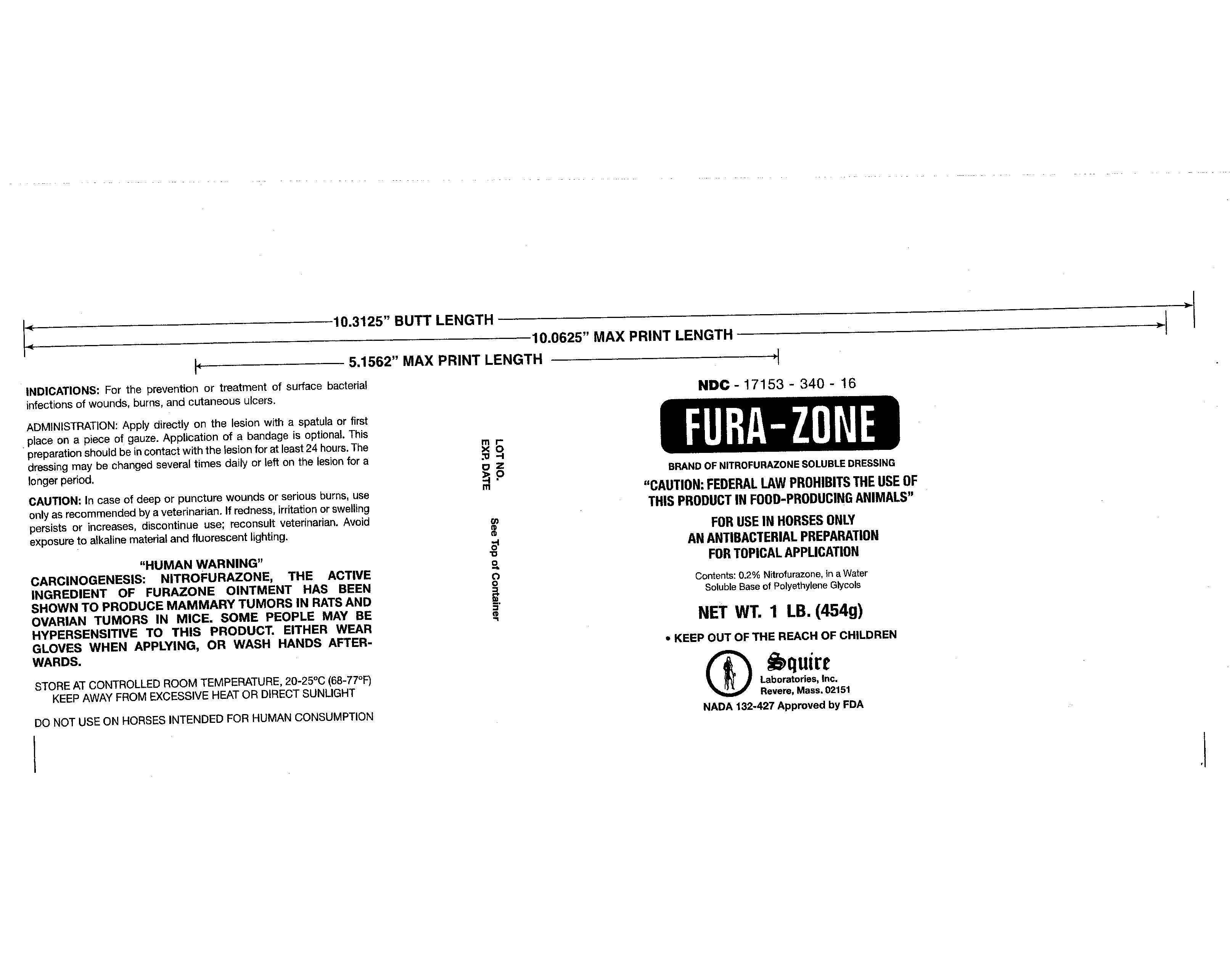 DRUG LABEL: Furazone
NDC: 17153-340 | Form: CREAM
Manufacturer: Squire Laboratories
Category: animal | Type: OTC ANIMAL DRUG LABEL
Date: 20141204

ACTIVE INGREDIENTS: NITROFURAZONE 0.000908 kg/1 kg
INACTIVE INGREDIENTS: POLYETHYLENE GLYCOL 400 0.298732 kg/1 kg; POLYETHYLENE GLYCOL 3350 0.15436 kg/1 kg

Furazone

INDICATIONS: For the prevention or treatment of surface bacterial
infections of wounds, burns, and cutaneous ulcers.

ADMINISTRATION: Apply directly on the lesion with a spatula or first
place on a piece of gauze. Application of a bandage is optional. This
preparation should be in contact with the lesion for at least 24 hours.
The dressing may be changed several times daily or left on the lesion for
a longer period.

CAUTION: In case of deep or puncture wounds or serious burns, use
only as recommended by a veterinarian. If redness, irritation or swelling
persists or increases, discontinue use; reconsult veterinarian. Avoid
exposure to alkaline material and fluorescent lighting.

Furazone Warnings

“HUMAN WARNING”
CARCINOGENESIS: NITROFURAZONE, THE ACTIVE INGREDIENT OF
FURA-ZONE OINTMENT HAS BEEN SHOWN TO PRODUCE MAMMARY
TUMORS IN RATS AND OVARIAN TUMORS IN MICE. SOME PEOPLE
MAY BE HYPERSENSITIVE TO THIS PRODUCT. EITHER WEAR GLOVES
WHEN APPLYING, OR WASH HANDS AFTERWARDS.

STORE AT CONTROLLED ROOM TEMPERATURE, 20-25⁰C (68-77⁰F)
KEEP AWAY FROM EXCESSIVE HEAT OR DIRECT SUNLIGHT

DO NOT USE ON HORSES INTENDED FOR HUMAN CONSUMPTION

Furazone

Furazone Label